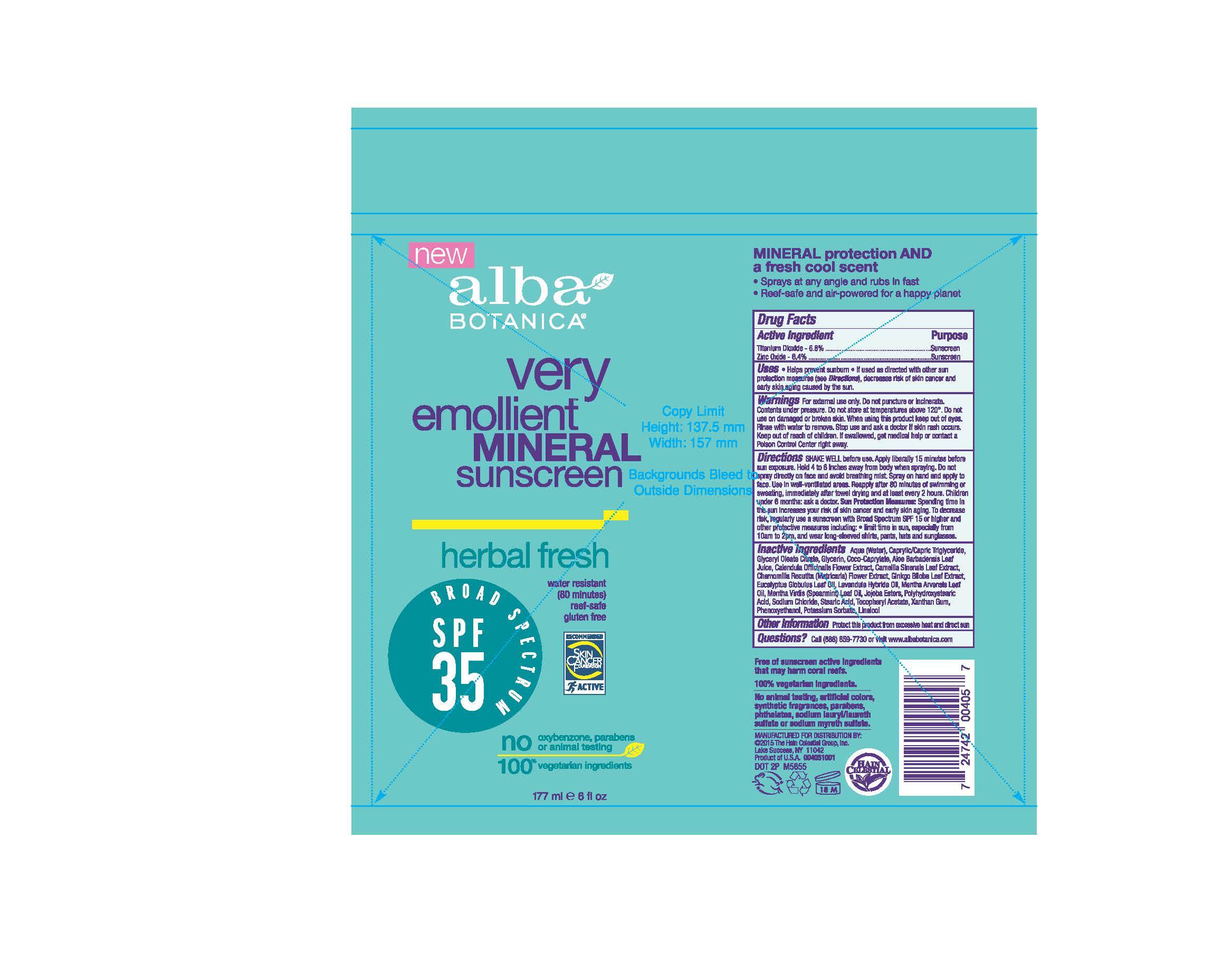 DRUG LABEL: AL0040500 Alba VE Mineral Sunscreen Herbal Fresh SPF35
NDC: 61995-2405 | Form: SPRAY
Manufacturer: The Hain Celestial Group, Inc.
Category: otc | Type: HUMAN OTC DRUG LABEL
Date: 20210205

ACTIVE INGREDIENTS: ZINC OXIDE 6.4 g/100 g; TITANIUM DIOXIDE 6.8 g/100 g
INACTIVE INGREDIENTS: LAVANDIN OIL; CALENDULA OFFICINALIS FLOWER; HYDROGENATED JOJOBA OIL, RANDOMIZED; COCO-CAPRYLATE; MATRICARIA RECUTITA; GLYCERYL OLEATE; XANTHAN GUM; POLYHYDROXYSTEARIC ACID (2300 MW); MEDIUM-CHAIN TRIGLYCERIDES; .ALPHA.-TOCOPHEROL ACETATE; PHENOXYETHANOL; POTASSIUM SORBATE; ALOE VERA LEAF; GLYCERIN; WATER; GREEN TEA LEAF; GINKGO; SODIUM CHLORIDE; STEARIC ACID; EUCALYPTUS OIL; MENTHA ARVENSIS LEAF OIL; SPEARMINT OIL

Alba Botanica VEBL Mineral Sunscreen Herbal Fresh SPF 35 Spray

Active Ingredient

Zinc Oxide 6.4%

Titanium Dioxide 6.8%

PURPOSE

Sunscreen

WARNINGS

For external use only. Do not puncture or incinerate. Contents under preassure. Do not store at temperature above 120°. Do not use on damaged or broken skin. When using this product keep out of eyes. Rinse with water to remove. Stop using and ask a doctor if skin rash occurs.

Keep out of reach of children. If swallowed get medical help or contact Poison Center right away.

INACTIVE INGREDIENT

Aqua (Water), Caprylic Capric Triglyceride, Glyceryl Oleate Citrate, Glycerin, Coco-Caprylate, Aloe Barbadensis Leaf Juice, Calendula Officinalis Flower Extract, Camellia Sinensis Leaf Extract, Camomilla Recutita (Matricaria) Flower Extract, Ginkgo Biloba Leaf Extract, Eucalyptus Globulus Leaf Oil, Lavandula Hybrida Oil, Mentha Arvensis Leaf Oil, Mentha Verdis (Spearmint) Leaf Oil, Jojoba Esters, Polyhydroxystearic Acid, Tocopheryl Acetate, Sodium Chloride, Stearic Acid, Xanthan Gum, Phenoxyethanol, Potassium Sorbate.

INDICATIONS AND USAGE

- Helps prevent sunburn.
- If used as directed with other sun protection measures (see Directions), decreases risk of skin cancer and early skin aging caused by the sun.

WHEN USING

SHAKE WELL before use. Apply liberally 15 minutes before sun explosure. Hold 4-6 inches away from body when spraying. Do not spray directly on face and avoid breathing mist. Spray on hand and apply to face. Use in well ventillated areas. Reapply after 80 minutes of swimming or sweating, immideately after towel drying and at least every 2 hours. Cildren under 6 months: ask doctor. Sun Protection Measures: Spending time in the sun increasis your risk of skin cancer and early skin aging. To decrease risk, regulary use a sunscreen with Broad Spectrum SPF 15 or higher and other preventive measures including: limit time in sun, especially from 10 am to 2 pm, and wear long-sleeved shirts, pants, hats and sunglasses.